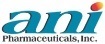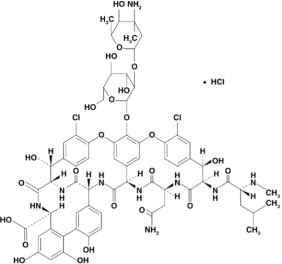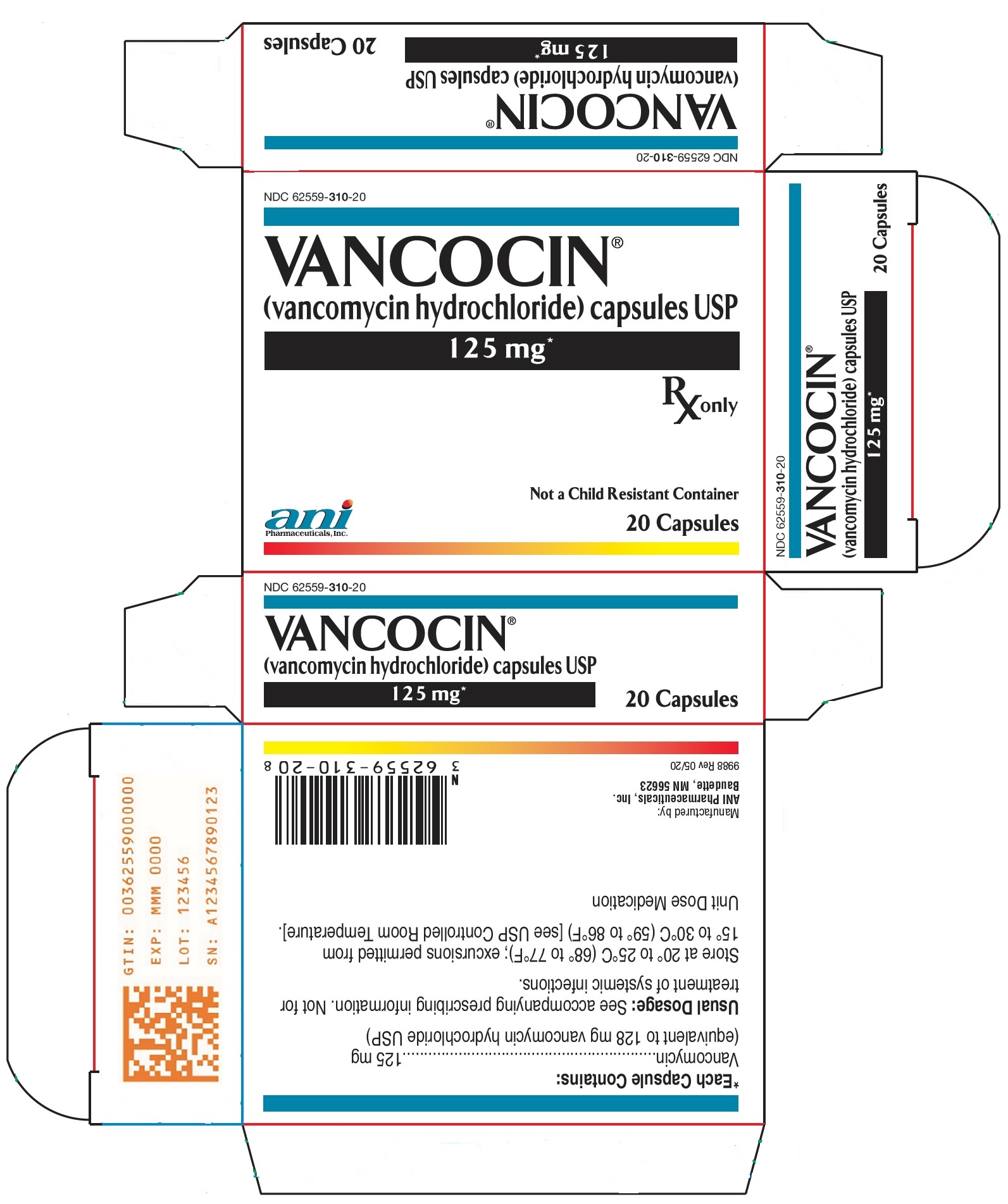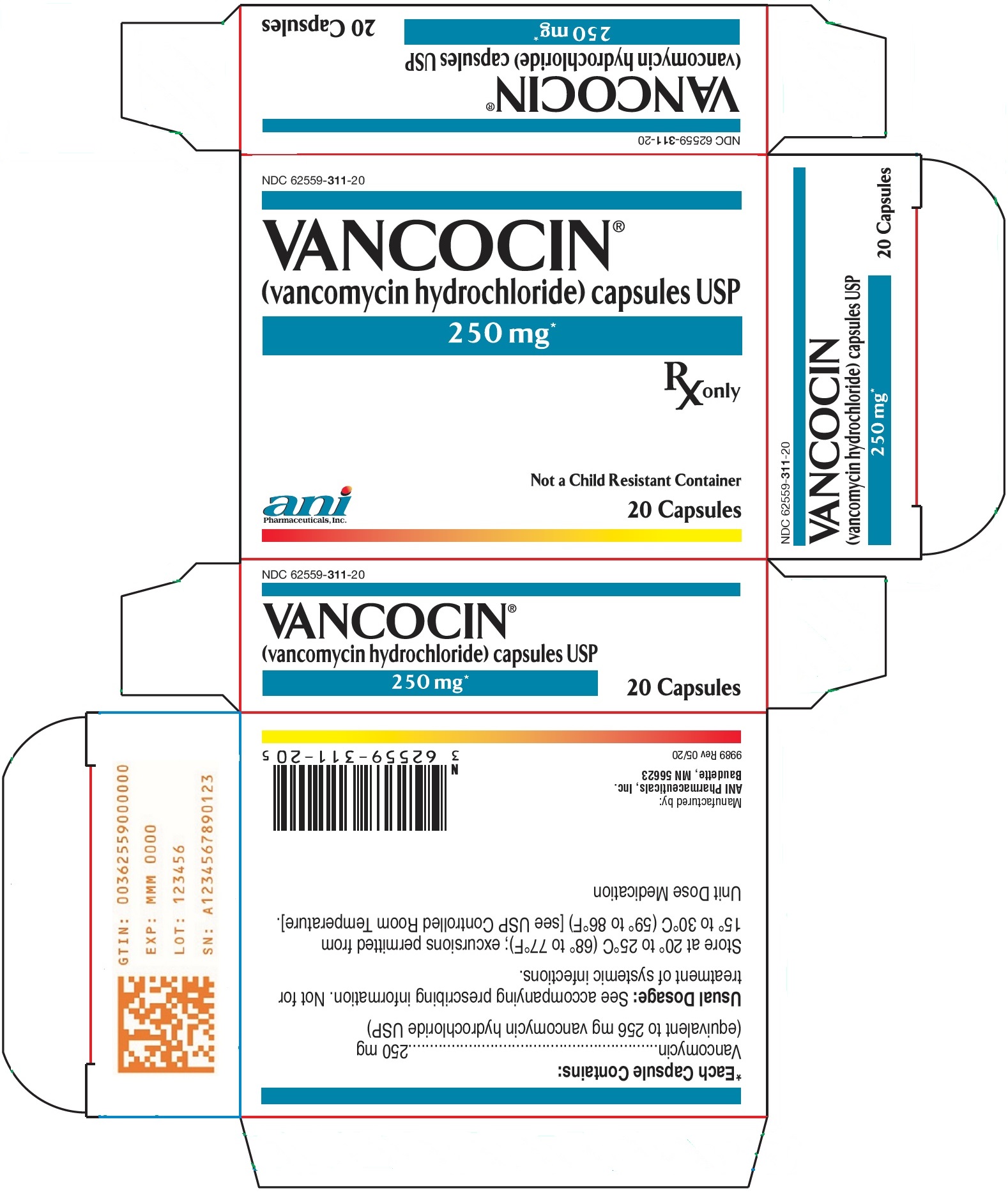 DRUG LABEL: Vancocin
NDC: 62559-310 | Form: CAPSULE
Manufacturer: ANI Pharmaceuticals, Inc.
Category: prescription | Type: HUMAN PRESCRIPTION DRUG LABEL
Date: 20251222

ACTIVE INGREDIENTS: VANCOMYCIN HYDROCHLORIDE 125 mg/1 1
INACTIVE INGREDIENTS: FD&C BLUE NO. 2; GELATIN, UNSPECIFIED; FERRIC OXIDE RED; FERRIC OXIDE YELLOW; POLYETHYLENE GLYCOL 6000; TITANIUM DIOXIDE

HIGHLIGHTS OF PRESCRIBING INFORMATION

These highlights do not include all the information needed to use VANCOCIN safely and effectively. See full prescribing information for VANCOCIN.
VANCOCIN® (vancomycin hydrochloride) capsules, for oral use
Initial U.S. Approval: 1986

1 INDICATIONS AND USAGE

VANCOCIN is a glycopeptide antibacterial indicated in adult and pediatric patients (less than 18 years of age) for the treatment of: (1)

- Clostridioides difficile-associated diarrhea
- Enterocolitis caused by Staphylococcus aureus (including methicillin-resistant strains)

Limitations of Use: (1) (5.1)

- Parenteral administration of vancomycin is not effective for the above infections; therefore, vancocin must be given orally for these infections.
- Orally administered VANCOCIN is not effective for other types of infections.

To reduce the development of drug-resistant bacteria and maintain the effectiveness of VANCOCIN and other antibacterial drugs, VANCOCIN should be used only to treat or prevent infections that are proven or strongly suspected to be caused by bacteria. (1)

2 DOSAGE AND ADMINISTRATION

- C. difficile-associated diarrhea:
  - Adult Patients (18 years of age or greater): 125 mg orally 4 times daily for 10 days. (2.1)
  - Pediatric Patients (less than 18 years of age): 40 mg/kg in 3 or 4 divided doses for 7 to 10 days. The total daily dosage should not exceed 2 g. (2.2)
- Staphylococcal enterocolitis:
  - Adult Patients (18 years of age or greater): 500 mg to 2 g orally in 3 or 4 divided doses for 7 to 10 days. (2.1)
  - Pediatric Patients (less than 18 years of age): 40 mg/kg in 3 or 4 divided doses for 7 to 10 days. The total daily dosage should not exceed 2 g. (2.2)

3 DOSAGE FORMS AND STRENGTHS

125 mg capsules and 250 mg capsules (3)

4 CONTRAINDICATIONS

Hypersensitivity to vancomycin (4)

5 WARNINGS AND PRECAUTIONS

- VANCOCIN must be given orally for treatment of staphylococcal enterocolitis and C. difficile-associated diarrhea. Orally administered VANCOCIN is not effective for other types of infections. (5.1)
- Clinically significant serum concentrations have been reported in some patients who have taken multiple oral doses of VANCOCIN for active C. difficile-associated diarrhea. Monitoring of serum concentrations may be appropriate in some instances. (5.2)
- Nephrotoxicity has occurred following oral VANCOCIN therapy and can occur either during or after completion of therapy. The risk is increased in geriatric patients. (5.3) Monitor renal function.
- Ototoxicity has occurred in patients receiving VANCOCIN. (5.4) Assessment of auditory function may be appropriate in some instances.
- Severe Dermatologic Reactions: Discontinue VANCOCIN at the first appearance of skin rashes, mucosal lesions, or blisters. (5.5)
- Prescribing VANCOCIN in the absence of a proven or strongly suspected bacterial infection is unlikely to provide benefit to the patient and increases the risk of the development of drug resistant bacteria. (5.6)

6 ADVERSE REACTIONS

The most common adverse reactions (≥ 10%) were nausea (17%), abdominal pain (15%), and hypokalemia (13%). (6.1)

To report SUSPECTED ADVERSE REACTIONS, contact ANI Pharmaceuticals, Inc. at 1-855-204-1431 or FDA at 1-800-FDA-1088 or www.fda.gov/medwatch.

8 USE IN SPECIFIC POPULATIONS

Geriatrics: In patients >65 years of age, including those with normal renal function prior to treatment, renal function should be monitored during and following treatment with VANCOCIN to detect potential vancomycin induced nephrotoxicity. (5.3) (6.1) (8.5) (14.1)

FULL PRESCRIBING INFORMATION

1 INDICATIONS AND USAGE

VANCOCIN is indicated for the treatment of Clostridioides difficile-associated diarrhea. VANCOCIN is also used for the treatment of enterocolitis caused by Staphylococcus aureus (including methicillin-resistant strains) in adult and pediatric patients less than 18 years of age.

Limitations of Use

- Parenteral administration of vancomycin is not effective for the above infections; therefore, VANCOCIN must be given orally for these infections.
- Orally administered VANCOCIN is not effective for other types of infections.

To reduce the development of drug-resistant bacteria and maintain the effectiveness of VANCOCIN and other antibacterial drugs, VANCOCIN should be used only to treat or prevent infections that are proven or strongly suspected to be caused by susceptible bacteria. When culture and susceptibility information are available, they should be considered in selecting or modifying antibacterial therapy. In the absence of such data, local epidemiology and susceptibility patterns may contribute to the empiric selection of therapy.

2 DOSAGE AND ADMINISTRATION

2.1 Adults

VANCOCIN capsules are used in treating C. difficile-associated diarrhea and staphylococcal enterocolitis.

- C. difficile-associated diarrhea: The recommended dose is 125 mg administered orally 4 times daily for 10 days.
- Staphylococcal enterocolitis: Total daily dosage is 500 mg to 2 g administered orally in 3 or 4 divided doses for 7 to 10 days.

2.2 Pediatric Patients (less than 18 years of age)

For both C. difficile-associated diarrhea and staphylococcal enterocolitis, the usual daily dosage is 40 mg/kg in 3 or 4 divided doses for 7 to 10 days. The total daily dosage should not exceed 2 g.

3 DOSAGE FORMS AND STRENGTHS

VANCOCIN 125 mg (equivalent to vancomycin) capsules have an opaque blue cap and opaque brown body imprinted with “3125” on the cap and “VANCOCIN HCL 125 MG” on the body in white ink.

VANCOCIN 250 mg (equivalent to vancomycin) capsules have an opaque blue cap and opaque lavender body imprinted with “3126” on the cap and “VANCOCIN HCL 250 MG” on the body in white ink.

4 CONTRAINDICATIONS

VANCOCIN is contraindicated in patients with known hypersensitivity to vancomycin.

5 WARNINGS AND PRECAUTIONS

5.1 Oral Use Only

VANCOCIN for the treatment of colitis is for oral use only and is not systemically absorbed. VANCOCIN must be given orally for treatment of staphylococcal enterocolitis and Clostridioides difficile-associated diarrhea. Orally administered VANCOCIN is not effective for other types of infections.

Parenteral administration of vancomycin is not effective for treatment of staphylococcal enterocolitis and C. difficile-associated diarrhea. If parenteral vancomycin therapy is desired, use an intravenous preparation of vancomycin and consult the package insert accompanying that preparation.

5.2 Potential for Systemic Absorption

Clinically significant serum concentrations have been reported in some patients who have taken multiple oral doses of VANCOCIN for active C. difficile-associated diarrhea. Some patients with inflammatory disorders of the intestinal mucosa also may have significant systemic absorption of vancomycin. These patients may be at risk for the development of adverse reactions associated with higher doses of VANCOCIN; therefore, monitoring of serum concentrations of vancomycin may be appropriate in some instances, e.g., in patients with renal insufficiency and/or colitis or in those receiving concomitant therapy with an aminoglycoside antibiotic.

5.3 Nephrotoxicity

Nephrotoxicity (e.g., reports of renal failure, renal impairment, blood creatinine increased) has occurred following oral VANCOCIN therapy in randomized controlled clinical studies, and can occur either during or after completion of therapy. The risk of nephrotoxicity is increased in patients >65 years of age [see Adverse Reactions (6.1) and Use in Specific Populations (8.5)].

In patients >65 years of age, including those with normal renal function prior to treatment, renal function should be monitored during and following treatment with VANCOCIN to detect potential vancomycin induced nephrotoxicity.

5.4 Ototoxicity

Ototoxicity has occurred in patients receiving vancomycin. It may be transient or permanent. It has been reported mostly in patients who have been given excessive intravenous doses, who have an underlying hearing loss, or who are receiving concomitant therapy with another ototoxic agent, such as an aminoglycoside. Serial tests of auditory function may be helpful in order to minimize the risk of ototoxicity [see Adverse Reactions (6.2)].

5.5 Severe Dermatologic Reactions

Severe dermatologic reactions such as toxic epidermal necrolysis (TEN), Stevens-Johnson syndrome (SJS), drug reaction with eosinophilia and systemic symptoms (DRESS), acute generalized exanthematous pustulosis (AGEP), and linear IgA bullous dermatosis (LABD) have been reported in association with the use of vancomycin. Cutaneous signs or symptoms reported include skin rashes, mucosal lesions, and blisters.

Discontinue VANCOCIN at the first appearance of signs and symptoms of TEN, SJS, DRESS, AGEP, or LABD.

5.6 Development of Drug-Resistant Bacteria

Prescribing VANCOCIN in the absence of a proven or strongly suspected bacterial infection or a prophylactic indication is unlikely to provide benefit to the patient and increases the risk of the development of drug resistant bacteria.

6 ADVERSE REACTIONS

6.1 Clinical Trials Experience

Because clinical studies are conducted under widely varying conditions, adverse reaction rates observed in the clinical studies of a drug cannot be directly compared to rates in the clinical studies of another drug and may not reflect the rates observed in practice.

The data described below reflect exposure to VANCOCIN in 260 adult subjects in two Phase 3 clinical trials for the treatment of diarrhea associated with C. difficile. In both trials, subjects received VANCOCIN 125 mg orally four times daily. The mean duration of treatment was 9.4 days. The median age of patients was 67, ranging between 19 and 96 years of age. Patients were predominantly Caucasian (93%) and 52% were male.

Adverse reactions occurring in ≥5% of VANCOCIN-treated subjects are shown in Table 1. The most common adverse reactions associated with VANCOCIN (≥10%) were nausea, abdominal pain, and hypokalemia.

Table 1: Common (≥5%) Adverse Reactionsa for VANCOCIN Reported in Clinical Trials for Treatment of Diarrhea Associated with C. difficile
System/Organ Class | Adverse Reaction | VANCOCIN % (N=260)
Gastrointestinal disorders | Nausea Abdominal pain Vomiting Diarrhea Flatulence | 17 15 9 9 8
General disorders and administration site conditions | Pyrexia Edema peripheral Fatigue | 9 6 5
Infections and infestations | Urinary tract infection | 8
Metabolism and nutrition disorders | Hypokalemia | 13
Musculoskeletal and connective tissue disorders | Back pain | 6
Nervous system disorders | Headache | 7
a Adverse reaction rates were derived from the incidence of treatment-emergent adverse events.

Nephrotoxicity (e.g., reports of renal failure, renal impairment, blood creatinine increased) occurred in 5% of subjects treated with VANCOCIN. Nephrotoxicity following VANCOCIN typically first occurred within one week after completion of treatment (median day of onset was Day 16). Nephrotoxicity following VANCOCIN occurred in 6% of subjects >65 years of age and 3% of subjects ≤65 years of age [see Warnings and Precautions (5.3)].

The incidences of hypokalemia, urinary tract infection, peripheral edema, insomnia, constipation, anemia, depression, vomiting, and hypotension were higher among subjects >65 years of age than in subjects ≤65 years of age [see Use in Specific Populations (8.5)].

Discontinuation of study drug due to adverse events occurred in 7% of subjects treated with VANCOCIN. The most common adverse events leading to discontinuation of VANCOCIN were C. difficile colitis (<1%), nausea (<1%), and vomiting (<1%).

6.2 Postmarketing Experience

The following adverse reactions have been identified during post-approval use of VANCOCIN. Because these reactions are reported voluntarily from a population of uncertain size, it is not always possible to reliably estimate their frequency or establish a causal relationship to drug exposure.

Ototoxicity: Cases of hearing loss associated with intravenously administered vancomycin have been reported. Most of these patients had kidney dysfunction or a preexisting hearing loss or were receiving concomitant treatment with an ototoxic drug [see Warnings and Precautions (5.4)]. Vertigo, dizziness, and tinnitus have been reported.

Skin and Subcutaneous Tissue Disorders: Severe dermatologic reactions such as toxic epidermal necrolysis (TEN), Stevens-Johnson syndrome (SJS), drug reaction with eosinophilia and systemic symptoms (DRESS), acute generalized exanthematous pustulosis (AGEP), and linear IgA bullous dermatosis (LABD) [see Warnings and Precautions (5.5)], rashes (including exfoliative dermatitis).

Hematopoietic: Reversible neutropenia, usually starting 1 week or more after onset of intravenous therapy with vancomycin or after a total dose of more than 25 g, has been reported for several dozen patients. Neutropenia appears to be promptly reversible when vancomycin is discontinued. Thrombocytopenia has been reported.

Miscellaneous: Patients have been reported to have had anaphylaxis, drug fever, chills, nausea, eosinophilia, and cases of vasculitis in association with the administration of vancomycin.

A condition has been reported that is similar to the IV-induced syndrome with symptoms consistent with anaphylactoid reactions, including hypotension, wheezing, dyspnea, urticaria, pruritus, flushing of the upper body (“vancomycin infusion reaction”), pain and muscle spasm of the chest and back. These reactions usually resolve within 20 minutes but may persist for several hours.

7 DRUG INTERACTIONS

No drug interaction studies have been conducted.

8 USE IN SPECIFIC POPULATIONS

8.1 Pregnancy

Risk Summary

Systemic absorption of vancomycin is low following oral administration of VANCOCIN; however, absorption may vary depending on various factors [see Clinical Pharmacology (12.3)]. There are no available data on vancomycin use in pregnant women to assess a risk of major birth defects or miscarriage. Available published data on intravenous vancomycin use in pregnancy during the second and third trimesters have not shown an association with adverse maternal or fetal outcomes (see Data).

Vancomycin did not show adverse developmental effects when administered intravenously to pregnant rats and rabbits during organogenesis at doses less than or equal to the recommended maximum human dose (see Data).

Data

Human Data
There are no available data on first trimester use of vancomycin in pregnant women to assess a risk of major birth defects or miscarriage.

A published study evaluated hearing loss and nephrotoxicity in infants of 10 pregnant intravenous drug users treated with intravenous vancomycin for suspected or documented methicillin-resistant Staphylococcal aureus in the second or third trimester. The comparison groups were 10 uninfected non-intravenous drug-dependent patients who received no treatment and 10 uninfected untreated intravenous drug-dependent patients. No infant in the vancomycin exposed group had abnormal sensorineural hearing at 3 months of age or nephrotoxicity.

A published prospective study assessed outcomes in 55 pregnant women with a positive Group B streptococcus culture and a high-risk penicillin allergy with resistance to clindamycin or unknown sensitivity who were administered intravenous vancomycin at the time of delivery. Vancomycin dosing ranged from the standard dose of 1 g intravenously every 12 hours to a dose of 20 mg/kg intravenously every 8 hours (maximum individual dose 2 g). No major adverse reactions were recorded either in the mothers or their newborns. None of the newborns had sensorineural hearing loss. Neonatal renal function was not examined, but all of the newborns were discharged in good condition.

Animal Data
Vancomycin did not cause fetal malformation when administered intravenously during organogenesis to pregnant rats (gestation days 6 to 15) and rabbits (gestation days 6 to 18) at the equivalent recommended maximum human dose of 200 mg/kg/day to rats or 120 mg/kg/day to rabbits. No effects on fetal weight or development were seen in rats at the highest dose tested or in rabbits given 80 mg/kg/day (approximately 1 and 0.8 880 mg/m2 or 0.74 times the recommended maximum human dose based on body surface area). Maternal toxicity was observed in rats (at doses 120 mg/kg and above) and rabbits (at 80 mg/kg and above).

8.2 Lactation

Risk Summary

There are no data on the presence of vancomycin in human milk, the effects on the breastfed infant, or the effect on milk production following oral administration. Systemic absorption of vancomycin is low following oral administration of VANCOCIN [see Clinical Pharmacology (12.3)]; therefore, it is unlikely to result in clinically relevant exposure in breastfeeding infants. The developmental and health benefits of breastfeeding should be considered along with the mother’s clinical need for VANCOCIN and any potential adverse effects on the breastfed infant from VANCOCIN or from the underlying maternal condition.

8.4 Pediatric Use

VANCOCIN is indicated in pediatric patients less than 18 years of age for the treatment of C. difficile-associated diarrhea and enterocolitis caused by S. aureus (including methicillin-resistant strains) [see Indications and Usage (1) and Dosage and Administration (2.2)].

8.5 Geriatric Use

In clinical trials, 54% of VANCOCIN-treated subjects were >65 years of age. Of these, 40% were between the ages of >65 and 75, and 60% were >75 years of age.

Clinical studies with VANCOCIN in diarrhea associated with Clostridioides difficile have demonstrated that geriatric subjects are at increased risk of developing nephrotoxicity following treatment with oral VANCOCIN, which may occur during or after completion of therapy. In patients >65 years of age, including those with normal renal function prior to treatment, renal function should be monitored during and following treatment with VANCOCIN to detect potential vancomycin induced nephrotoxicity [see Warnings and Precautions (5.3), Adverse Reactions (6.1), and Clinical Studies (14.1)].

Patients >65 years of age may take longer to respond to therapy compared to patients ≤65 years of age [see Clinical Studies (14.1)]. Clinicians should be aware of the importance of appropriate duration of VANCOCIN treatment in patients >65 years of age and not discontinue or switch to alternative treatment prematurely.

10 OVERDOSAGE

Supportive care is advised, with maintenance of glomerular filtration. Vancomycin is poorly removed by dialysis. Hemofiltration and hemoperfusion with polysulfone resin have been reported to result in increased vancomycin clearance.

To obtain current information about the treatment of overdose, contact a certified Poison Control Center (1-800-222-1222 or www.poison.org). In managing overdosage, consider the possibility of multiple drug overdoses, interaction among drugs, and unusual drug kinetics.

11 DESCRIPTION

VANCOCIN capsules for oral administration contain chromatographically purified vancomycin hydrochloride, a tricyclic glycopeptide antibiotic derived from Amycolatopsis orientalis (formerly Nocardia orientalis), which has the chemical formula C66H75Cl2N9O24•HCl. The molecular weight of vancomycin hydrochloride is 1485.73; 500 mg of the base is equivalent to 0.34 mmol.

Each capsule contains 125 mg vancomycin (equivalent to 128 mg vancomycin hydrochloride) or 250 mg vancomycin (equivalent to 256 mg vancomycin hydrochloride). The capsules also contain FD&C Blue No. 2, gelatin, iron oxide, polyethylene glycol, titanium dioxide, and other inactive ingredients.

Vancomycin hydrochloride has the structural formula:

12 CLINICAL PHARMACOLOGY

12.1 Mechanism of Action

Vancomycin is an antibacterial drug [see Microbiology (12.4)].

12.3 Pharmacokinetics

Vancomycin is poorly absorbed after oral administration. During multiple dosing of 250 mg every 8 hours for 7 doses, fecal concentrations of vancomycin in volunteers exceeded 100 mg/kg in the majority of samples. No blood concentrations were detected and urinary recovery did not exceed 0.76%. In anephric subjects with no inflammatory bowel disease who received vancomycin oral solution 2 g for 16 days, blood concentrations of vancomycin were less than or equal to 0.66 mcg/mL in 2 of 5 subjects. No measurable blood concentrations were attained in the other 3 subjects. Following doses of 2 g daily, concentrations of drug were >3100 mg/kg in the feces and <1 mcg/mL in the serum of subjects with normal renal function who had C. difficile-associated diarrhea. After multiple-dose oral administration of vancomycin, measurable serum concentrations may occur in patients with active C. difficile-associated diarrhea, and, in the presence of renal impairment, the possibility of accumulation exists. It should be noted that the total systemic and renal clearances of vancomycin are reduced in the elderly [see Use in Specific Populations (8.5)].

12.4 Microbiology

Mechanism of action

The bactericidal action of vancomycin against Staphylococcus aureus and the vegetative cells of Clostridioides difficile results primarily from inhibition of cell-wall biosynthesis. In addition, vancomycin alters bacterial-cell-membrane permeability and RNA synthesis.

Resistance

Staphylococcus aureus
S. aureus isolates with vancomycin minimal inhibitory concentrations (MICs) as high as 1024 mcg/mL have been reported.
The exact mechanism of this resistance is not clear but is believed to be due to cell wall thickening and potentially the transfer of genetic material.
Clostridioides difficile
Isolates of C. difficile generally have vancomycin MICs of <1 mcg/mL, however vancomycin MICs ranging from 4 mcg/mL to 16 mcg/mL have been reported. The mechanism which mediates C. difficile's decreased susceptibility to vancomycin has not been fully elucidated.

Vancomycin has been shown to be active against most isolates of the following microorganisms, both in vitro and in clinical infections [see Indications and Usage (1)].

Gram-positive bacteria

Staphylococcus aureus (including methicillin-resistant isolates) associated with enterocolitis.

Anaerobic gram-positive bacteria

Clostridioides difficile isolates associated with C. difficile associated diarrhea.

13 NONCLINICAL TOXICOLOGY

13.1 Carcinogenesis, Mutagenesis, Impairment of Fertility

No long-term carcinogenesis studies in animals have been conducted.

At concentrations up to 1000 mcg/mL, vancomycin had no mutagenic effect in vitro in the mouse lymphoma forward mutation assay or the primary rat hepatocyte unscheduled DNA synthesis assay. The concentrations tested in vitro were above the peak plasma vancomycin concentrations of 20 to 40 mcg/mL usually achieved in humans after slow infusion of the maximum recommended dose of 1 g. Vancomycin had no mutagenic effect in vivo in the Chinese hamster sister chromatid exchange assay (400 mg/kg IP) or the mouse micronucleus assay (800 mg/kg IP).

No definitive fertility studies have been conducted.

14 CLINICAL STUDIES

14.1 Diarrhea Associated with Clostridioides difficile

In two trials, VANCOCIN 125 mg orally four times daily for 10 days was evaluated in 266 adult subjects with C. difficile-associated diarrhea (CDAD). Enrolled subjects were 18 years of age or older and received no more than 48 hours of treatment with oral VANCOCIN or oral/intravenous metronidazole in the 5 days preceding enrollment. CDAD was defined as ≥3 loose or watery bowel movements within the 24 hours preceding enrollment, and the presence of either C. difficile toxin A or B, or pseudomembranes on endoscopy within the 72 hours preceding enrollment. Subjects with fulminant C. difficile disease, sepsis with hypotension, ileus, peritoneal signs or severe hepatic disease were excluded.

Efficacy analyses were performed on the Full Analysis Set (FAS), which included randomized subjects who received at least one dose of VANCOCIN and had any post-dosing investigator evaluation data (N=259; 134 in Trial 1 and 125 in Trial 2).

The demographic profile and baseline CDAD characteristics of enrolled subjects were similar in the two trials. VANCOCIN-treated subjects had a median age of 67 years, were mainly white (93%), and male (52%). CDAD was classified as severe (defined as 10 or more unformed bowel movements per day or WBC ≥15000/mm^3) in 25% of subjects, and 47% were previously treated for CDAD.

Efficacy was assessed by using clinical success, defined as diarrhea resolution and the absence of severe abdominal discomfort due to CDAD, on Day 10. An additional efficacy endpoint was the time to resolution of diarrhea, defined as the beginning of diarrhea resolution that was sustained through the end of the prescribed active treatment period.

The results for clinical success for VANCOCIN-treated subjects in both trials are shown in Table 2.

Table 2: Clinical Success Rates (Full Analysis Set)
 | Clinical Success Rate | 95% Confidence Interval
 | VANCOCIN % (N)
Trial 1 | 81.3 (134) | (74.4, 88.3)
Trial 2 | 80.8 (125) | (73.5, 88.1)

The median time to resolution of diarrhea was 5 days and 4 days in Trial 1 and Trial 2, respectively. For subjects older than 65 years of age, the median time to resolution was 6 days and 4 days in Trial 1 and Trial 2, respectively. In subjects with diarrhea resolution at end-of-treatment with VANCOCIN, recurrence of CDAD during the following four weeks occurred in 25 of 107 (23%) and 18 of 102 (18%) in Trial 1 and Trial 2, respectively.

Restriction Endonuclease Analysis (REA) was used to identify C. difficile baseline isolates in the BI group. In Trial 1, the Vancocin-treated subjects were classified at baseline as follows 31 (23%) with BI strain, 69 (52%) with non-BI strain, and 34 (25%) with unknown strain. Clinical success rates were 87% for BI strain, 81% for non-BI strain, and 76% for unknown strain. In subjects with diarrhea resolution at end-of-treatment with VANCOCIN, recurrence of CDAD during the following four weeks occurred in 7 of 26 subjects with BI strain, 12 of 56 subjects with non-BI strain, and 6 of 25 subjects with unknown strain.

15 REFERENCES

1. Byrd RA., Gries CL, Buening M.: Developmental Toxicology Studies of Vancomycin Hydrochloride Administered Intravenously to Rats and Rabbits. Fundam Appl Toxicol 1994; 23: 590-597.

16 HOW SUPPLIED/STORAGE AND HANDLING

VANCOCIN (vancomycin hydrochloride) capsules USP are available in:

The 125 mg (equivalent to vancomycin) capsules have an opaque blue cap and opaque brown body imprinted with “3125” on the cap and “VANCOCIN HCL 125 MG” on the body in white ink. A carton contains 2 blister packs. Each blister pack contains 10 capsules for a total of 20 capsules per carton. NDC 62559-310-20.

The 250 mg (equivalent to vancomycin) capsules have an opaque blue cap and opaque lavender body imprinted with “3126” on the cap and “VANCOCIN HCL 250 MG” on the body in white ink. A carton contains 2 blister packs. Each blister pack contains 10 capsules for a total of 20 capsules per carton. NDC 62559-311-20.

Store at 20° to 25°C (68° to 77°F); excursions permitted from 15° to 30°C (59° to 86°F) [see USP Controlled Room Temperature].

17 PATIENT COUNSELING INFORMATION

Severe Dermatologic Reactions

Advise patients about the signs and symptoms of serious skin manifestations. Instruct patients to stop taking VANCOCIN immediately and promptly seek medical attention at the first signs or symptoms of skin rash, mucosal lesions or blisters [see Warnings and Precautions (5.5)].

Antibacterial Resistance

Patients should be counseled that antibacterial drugs including VANCOCIN should only be used to treat bacterial infections. They do not treat viral infections (e.g., the common cold). When VANCOCIN is prescribed to treat a bacterial infection, patients should be told that although it is common to feel better early in the course of therapy, the medication should be taken exactly as directed. Skipping doses or not completing the full course of therapy may (1) decrease the effectiveness of the immediate treatment and (2) increase the likelihood that bacteria will develop resistance and will not be treatable by VANCOCIN or other antibacterial drugs in the future.

VANCOCIN® is a registered U.S. trademark owned by ANI Pharmaceuticals, Inc.

Distributed by:
ANI Pharmaceuticals, Inc.
Baudette, MN 56623

Package/Label Display Panel

NDC 62559-310-20
VANCOCIN® (vancomycin hydrochloride) capsules USP
125 mg*
Rx only
Not a Child Resistant Container
20 Capsules

Package/Label Display Panel

NDC 62559-311-20
VANCOCIN® (vancomycin hydrochloride) capsules USP
250 mg*
Rx only
Not a Child Resistant Container
20 Capsules